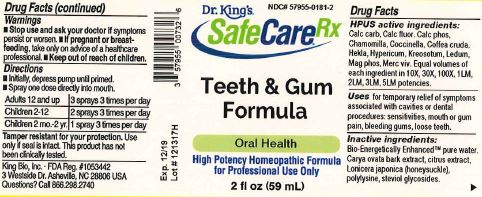 DRUG LABEL: Teeth and Gum Formula
NDC: 57955-0181 | Form: LIQUID
Manufacturer: King Bio Inc.
Category: homeopathic | Type: HUMAN OTC DRUG LABEL
Date: 20180212

ACTIVE INGREDIENTS: OYSTER SHELL CALCIUM CARBONATE, CRUDE 10 [hp_X]/59 mL; CALCIUM FLUORIDE 10 [hp_X]/59 mL; TRIBASIC CALCIUM PHOSPHATE 10 [hp_X]/59 mL; MATRICARIA RECUTITA 10 [hp_X]/59 mL; COCCINELLA SEPTEMPUNCTATA 10 [hp_X]/59 mL; ARABICA COFFEE BEAN 10 [hp_X]/59 mL; HEKLA LAVA 10 [hp_X]/59 mL; HYPERICUM PERFORATUM 10 [hp_X]/59 mL; WOOD CREOSOTE 10 [hp_X]/59 mL; LEDUM PALUSTRE TWIG 10 [hp_X]/59 mL; MAGNESIUM PHOSPHATE, DIBASIC TRIHYDRATE 10 [hp_X]/59 mL; MERCURY 10 [hp_X]/59 mL
INACTIVE INGREDIENTS: WATER; CARYA OVATA BARK; CITRUS BIOFLAVONOIDS; LONICERA JAPONICA FLOWER; POLYEPSILON-LYSINE (4000 MW); REBAUDIOSIDE A

Teeth and Gum Formula

ACTIVE INGREDIENT

Drug Facts__________________________________________________________________________________________________________

HPUS active ingredients: Calc carb, Calc fluor, Calc phos, Chamomilla, Coccinella, Coffea cruda, Hekla, Hypericum, Kreosotum, Ledum, Mag phos, Merc viv.

Equal volumes of each ingredient in 10X, 30X, 100X, 1LM, 2LM, 3LM, 5LM potencies.

INDICATIONS AND USAGE

Uses for temporary relief of symptoms associated with cavities or dental procedures: sensitivities, mouth or gum pain, bleeding gums, loose teeth.

Inactive Ingredients:

Bio-Energetically Enhanced™ pure water, Carya ovata bark extract, citrus extract, Lonicera japonica (honeysuckle), polylysine, steviol glycosides.

Warnings

- Stop use and ask your doctor if symptoms persist or worsen.
- If pregnant or breast-feeding, take only on advice of a healthcare professional.

- Keep out of reach of children.

Directions

- Initially, depress pump until primed.
- Spray one dose directly into mouth.
- Adults 12 and up: 3 sprays 3 times per day
- Children (2-12 years): 2 sprays 3 times per day
- Children (2 mo-2 yr): 1 spray 3 times per day

OTHER SAFETY INFORMATION

Tamper resistant for your protection. Use only if safety seal is intact. This product has not been clinically tested.

PURPOSE

Uses for temporary relief of symptoms associated with cavities or dental procedures:

- sensitivities
- mouth or gum pain
- bleeding gums
- loose teeth